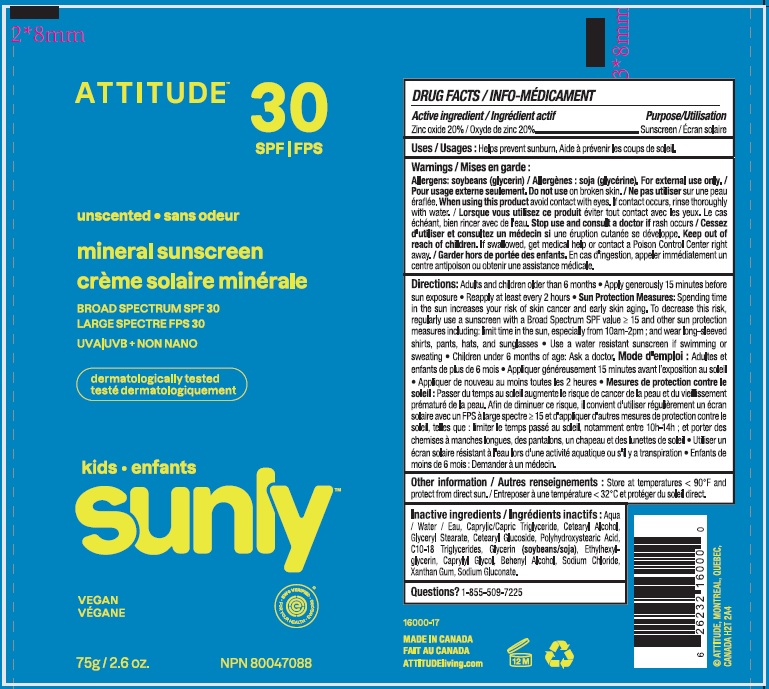 DRUG LABEL: Attitude Kids mineral sunscreen unscented SPF 30
NDC: 61649-160 | Form: CREAM
Manufacturer: 9055-7588 Québec Inc. DBA Attitude
Category: otc | Type: HUMAN OTC DRUG LABEL
Date: 20241201

ACTIVE INGREDIENTS: ZINC OXIDE 20 g/100 g
INACTIVE INGREDIENTS: WATER; MEDIUM-CHAIN TRIGLYCERIDES; POLYHYDROXYSTEARIC ACID (2300 MW); CETOSTEARYL ALCOHOL; GLYCERYL MONOSTEARATE; CETEARYL GLUCOSIDE; ETHYLHEXYLGLYCERIN; GLYCERIN; C10-18 TRIGLYCERIDES; DOCOSANOL; SODIUM CHLORIDE; XANTHAN GUM; CAPRYLYL GLYCOL; SODIUM GLUCONATE

Attitude Sunly Kids mineral sunscreen unscented SPF 30

Drug Facts

Active or medicinal ingredient

Zinc oxide (20%)

Purpose

Sunscreen

Use

Helps prevent sunburn

Warnings

Allergens: soybeans (glycerin). For external use only.

Do not use on broken skin.

Stop use and ask a doctor ifrash occurs.

When using this product keep out of eyes. If contact occurs, rinse thoroughly with water.

Keep out of reach of children.If swallowed, get medical help or contact a Poison Control Center right away.

Directions

Adults and children older than 6 months.

- Apply generously 15 minutes prior to sun exposure.
- Reapply every 2 hours or after swimming, towel drying, perspiring heavily, or washing .

Sun Protection Measures: Spending time in the sun increases your risk of skin cancer and early skin aging. To decrease this risk, regularly use a sunscreen with a Broad Spectrum SPF value of 15 or higher and other sun protection measures including: [Bullet] limit time in the sun, especially from 10 a.m.-2 p.m. wear long-sleeved shirts, pants, hats, and sunglasses.

Use a water resistant sunscreen if swimming or sweating.

Children under 6 months of age: Ask a doctor.

Inactive or non-medicinal ingredients

Aqua / Water / Eau, Caprylic/Capric Triglyceride, Cetearyl Glucoside, Glyceryl Stearate, Cetearyl Alcohol, Polyhydroxystearic Acid, C10-18 Triglycerides, Glycerin, Ethylhexylglycerin, Caprylyl Glycol, Behenyl Alcohol, Sodium Chloride, Xanthan Gum, Sodium Gluconate.

Other Information

Store at temperatures below 90°F and protect from direct sun.

RECENT MAJOR CHANGES

Dosage and Administration

Questions? 1-855-509-7225

PRINCIPAL DISPLAY PANEL - 75 g Tube Label

ATTITUDE®
natural care

30
SPF
SUNLY

unscented

broad spectrum SPF 30

UVA UVB + NON NANO

VEGAN

Dermatologically tested

EWG verified

NPN 80047088 ∙ 75 g / 2.6 OZ.